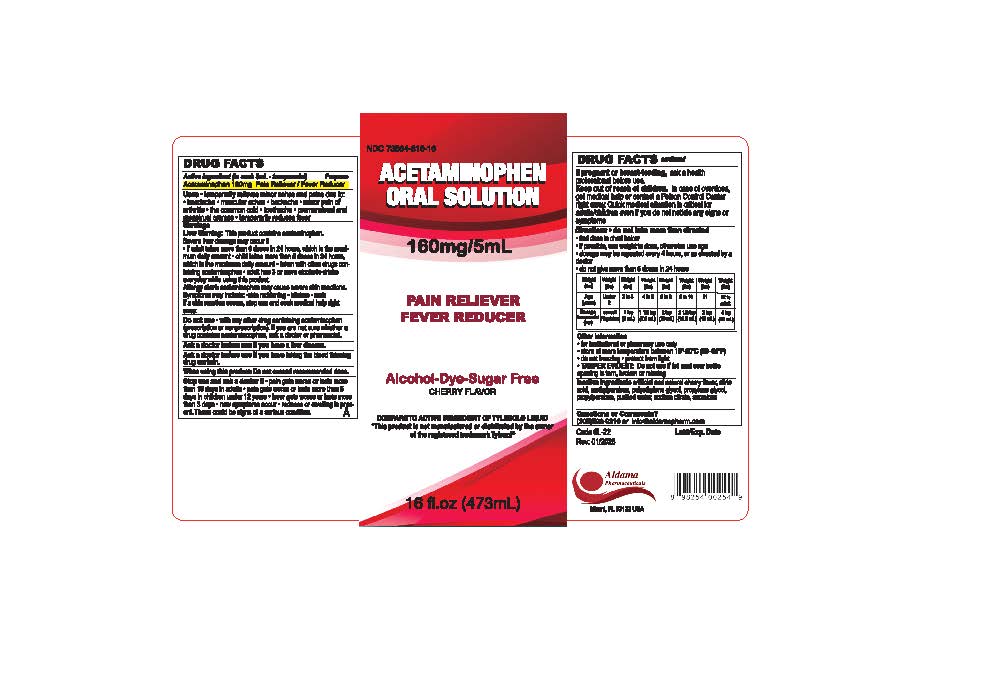 DRUG LABEL: Acetaminophen Oral Solution
NDC: 73564-816 | Form: SOLUTION
Manufacturer: Aldama Pharmaceuticals, Inc
Category: otc | Type: HUMAN OTC DRUG LABEL
Date: 20260118

ACTIVE INGREDIENTS: ACETAMINOPHEN 160 mg/5 mL
INACTIVE INGREDIENTS: WATER; SUCRALOSE; ANHYDROUS CITRIC ACID; POLYETHYLENE GLYCOL 350; PROPYLENE GLYCOL; METHYLPARABEN; PROPYLPARABEN; SODIUM CITRATE

Acetaminophen Oral Solution

Active ingredient (in each 5 mL-teaspoonful)

Acetaminophen 160mg

Purpose

Pain reliever/fever reducer

Uses

- Temporarily relieves minor aches and pains due to:
  - headache
  - muscular aches
  - backache
  - minor pain of arthritis
  - the common cold
  - toothache
  - premenstrual and menstrual cramps
  - temporarily reduces fever

Warnings

Liver warning

This product contains acetaminophen. Severe liver damage may occur if:

- if adults takes more than 6 doses in 24 hours, which is the maximum daily amount
- child takes more than 5 doses in 24 hours, which is the maximum daily amount
- taken with other drugs containing acetaminophen
- adult has 3 or more alcoholic drinks everyday while using the product.

Allergy alert:Acetaminophen may cause severe skin reactions. Symptoms may include:

- skin reddening
- blisters
- rash

If a skin reaction occurs, stop use and seek medical help right away.

Do not use

- with any other drug containing acetaminophen (prescription or nonprescription). If you are not sure whether a drug contains acetaminophen, ask a doctor or pharmacist.

Ask a doctor before use if your childhas liver disease

Ask a doctor before use if you have taking the blood thinning drug warfarin.

When using this product do not exceed recommended dose

Stop use and ask a doctor if

- pain gets worse or lasts more than 10 days in adults 5 days
- pain gets worse or lasts more than 5 days in children under 12 years
- fever gets worse or lasts more than 3 days
- new symptoms occur
- redness or swelling is present

These could be signs of a serious condition.

Keep out of reach of children.

In case of overdose, get medical help or conbtact a Poison Control Center right away. Quick medical attention is critical for adults/children even if you do not notice any signs or symptoms

If pregnant or breast-feeding

ask a health professional before use

Directions

- find dose in chart below
- if possible, use weight to dose, otherwise use age
- dosage may be repeated every 4 hours, or as directed by a doctor
- do not give more than 5 doses in 24 hours

Weight; (lbs) | Weight; (lbs) | Weight; (lbs) | Weight; (lbs) | Weight; (lbs) | Weight; (lbs) | Weight; (lbs) | Weight; (lbs)
Age; (years) | Under 2 | 2 to 3 | 4 to 5 | 6 to 8 | 9 to 10 | 11 | 12 to; adult
Dosage; teaspoonful (tsp) | consult Physician | 1 tsp; (5 ml) | 1 1/2 tsp; (7.5ml) | 2 tsp; (10 ml) | 2 1/2 tsp; (12.5ml) | 3 tsp; (15 ml) | 4 tsp; (20 ml)

Other information

- for institutional or pharmacy use only
- store at room temperature between 15-30°C (59-86°F)
- do not freezing
- protect from light
- TAMPER EVIDENT do not use if foil seal over bottle opening is torn, broken or missing

Inactive Ingredient

artificial and natural cherry flavor, citric acid, methylparaben, polyethylene glycol, propylene glycol, propylparaben, purified water, sodium citrate, sucralose

QUESTIONS

Question or Comments?

call 305-592-9216 or info@aldamapharm.com